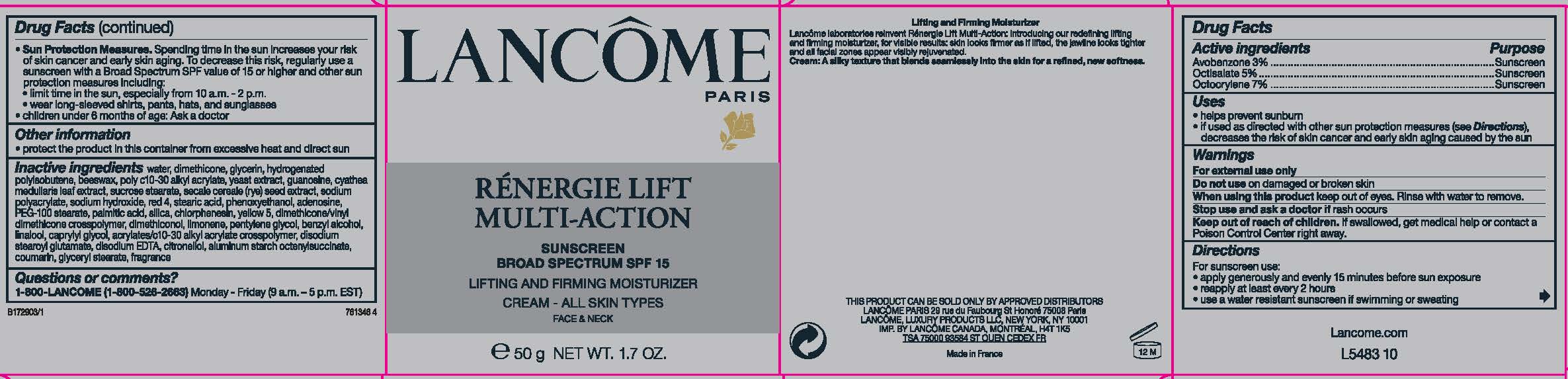 DRUG LABEL: Lancome Paris Renergie Lift MultiAction Sunscreen Broad Spectrum SPF 15 Lift and Firming Face and Neck All Skin Types
NDC: 49967-633 | Form: CREAM
Manufacturer: L'Oreal USA Products Inc
Category: otc | Type: HUMAN OTC DRUG LABEL
Date: 20231223

ACTIVE INGREDIENTS: Avobenzone 30 mg/1 g; Octisalate 50 mg/1 g; Octocrylene 70 mg/1 g
INACTIVE INGREDIENTS: WATER; DIMETHICONE; GLYCERIN; HYDROGENATED POLYBUTENE (1300 MW); YELLOW WAX; YEAST, UNSPECIFIED; GUANOSINE; CYATHEA MEDULLARIS LEAF; SUCROSE STEARATE; SODIUM POLYACRYLATE (2500000 MW); SODIUM HYDROXIDE; FD&C RED NO. 4; STEARIC ACID; PHENOXYETHANOL; ADENOSINE; PEG-100 STEARATE; PALMITIC ACID; SILICON DIOXIDE; CHLORPHENESIN; FD&C YELLOW NO. 5; DIMETHICONE/VINYL DIMETHICONE CROSSPOLYMER (HARD PARTICLE); DIMETHICONOL (100000 CST); LIMONENE, (+)-; PENTYLENE GLYCOL; BENZYL ALCOHOL; LINALOOL, (+/-)-; CAPRYLYL GLYCOL; CARBOMER INTERPOLYMER TYPE A (ALLYL SUCROSE CROSSLINKED); DISODIUM STEAROYL GLUTAMATE; EDETATE DISODIUM ANHYDROUS; .BETA.-CITRONELLOL, (R)-; ALUMINUM STARCH OCTENYLSUCCINATE; COUMARIN; GLYCERYL MONOSTEARATE

Drug Facts

Active ingredients

Avobenzone 3%

Octisalate 5%

Octocrylene 7%

Purpose

Sunscreen

Uses

- helps prevent sunburn
- if used as directed with other sun protection measures (see Directions), decreases the risk of skin cancer and early skin aging caused by the sun

Warnings

For external use only

Do not use

on damaged or broken skin

When using this product

keep out of eyes. Rinse with water to remove.

Stop use and ask a doctor if

rash occurs

Keep out of reach of children.

If swallowed, get medical help or contact a Poison Control Center right away.

Directions

For sunscreen use:

- apply generously and evenly 15 minutes before sun exposure
- reapply at least every 2 hours
- use a water resistant sunscreen if swimming or sweating
- Sun Protection Measures. Spending time in the sun increases your risk of skin cancer and early skin aging. To decrease this risk regularly use a sunscreen with a Broad Spectrum SPF value of 15 of higher and other sun protection measures including:
- limit time in the sun, especially from 10 a.m. - 2 p.m.
- wear long-sleeved shirts, pants, hats and sunglasses
- children under 6 months of age: Ask a doctor

Other information

- protect the product in this container from excessive heat and direct sun

Inactive ingredients

water, dimethicone, glycerin, hydrogenated polyisobutene, beeswax, poly C10-30 alkyl acrylate, yeast extract, guanosine, cyathea medullaris leaf extract, sucrose stearate, secale cereale (rye) seed extract, sodium polyacrylate, sodium hydroxide, red 4, stearic acid, phenoxyethanol, adenosine, PEG-100 stearate, palmitic acid, silica, chlorphenesin, yellow 5, dimethicone/vinyl dimethicone crosspolymer, dimethiconol, limonene, pentylene glycol, benzyl alcohol, linalool, caprylyl glycol, acrylates/C10-30 alkyl acrylate crosspolymer, disodium stearoyl glutamate, disodium EDTA, citronellol, aluminum starch octenylsuccinate, coumarin, glyceryl stearate, fragrance

Questions or comments?

1-800-LANCOME (1-800-526-2663) Monday - Friday (9 a.m. - 5 p.m. EST)